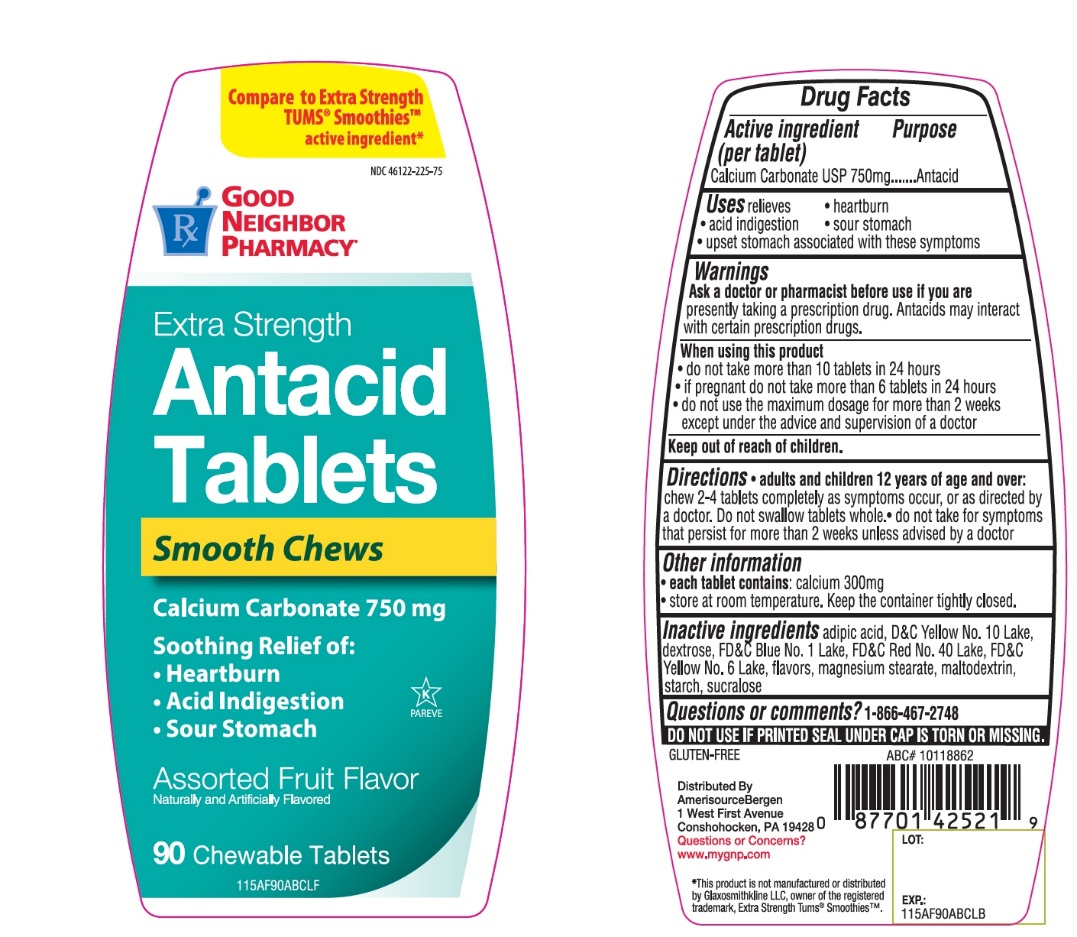 DRUG LABEL: Good Neighbor Extra Strength

NDC: 46122-225 | Form: TABLET, CHEWABLE
Manufacturer: AMERISOURCE BERGEN
Category: otc | Type: HUMAN OTC DRUG LABEL
Date: 20250709

ACTIVE INGREDIENTS: CALCIUM CARBONATE 750 mg/1 1
INACTIVE INGREDIENTS: ADIPIC ACID; D&C YELLOW NO. 10; DEXTROSE, UNSPECIFIED FORM; FD&C BLUE NO. 1; FD&C RED NO. 40; FD&C YELLOW NO. 6; MAGNESIUM STEARATE; MALTODEXTRIN; STARCH, CORN; SUCRALOSE

Extra Strength Smooth Antacid Assorted Fruit 90 Chewable Tablets

Active ingredient (per tablet)

Calcium Carbonate 750 mg

Purpose

Antacid

Uses

relieves:

- heartburn
- acid indigestion
- sour stomach
- upset stomach associated with these symptoms

Ask a doctor or pharmacist before use if you are

- presently taking a prescription drug. Antacids may interact with certain prescription drugs.

When using this product

- do not take more than 10 tablets in a 24-hours
- if pregnant do not take more than 6 tablets in 24 hours
- do not use the maximum dosage for more than 2 weeks except under the advice and supervision of a doctor.

Directions

- adults and children 12 years of age and over:chew 2-4 tablets completely as symptoms occur, or as directed by a doctor. Do not swallow tablets whole.
- do not take for symptoms that persists for more than 2 weeks unless advised by a doctor

Other information

- each tablet contains : elemental calcium 300 mg
- store at room temperature. Keep the container tightly closed.

SAFETY SEALED: DO NOT USE IF PRINTED SEAL UNDER CAP IS TORN OR MISSING

Inactive ingredients

adipic acid, D&C Yellow No. 10, dextrose, FD&C Blue No. 1 Lake, FD&C Red No. 40 Lake , FD&C Yellow No. 6 Lake , flavors, magnesium stearate, maltodextrin, starch, sucralose.

Questions or comments

1-866-467-2748

PRINCIPAL DISPLAY PANEL

GOOD NEIGHBOR PHARMACY

NDC 46122-225-75

Compare to Extra Strength Tums®Smoothies active ingredient*

EXTRA STRENGTH

Antacid Tablets

Smooth Chews

Calcium Carbonate 750 mg

Soothing Relief of:

- Heartburn
- Acid Indigestion
- Sour Stomach

Assorted Fruit Flavors

Naturally and Artificially Flavored
90 Chewable Tablets

GLUTEN-FREE
DISTRIBUTED. BY:

Amerisource Bergen

1 West first Avenue

Conshohocken, PA 19428

Questions or Concerns?

Visit www.mygnp.com

*This product is not manufactured or distributed by GlaxoSmithKline LLC, owner of the registered trademark, Extra Strength Tums® Smoothies.